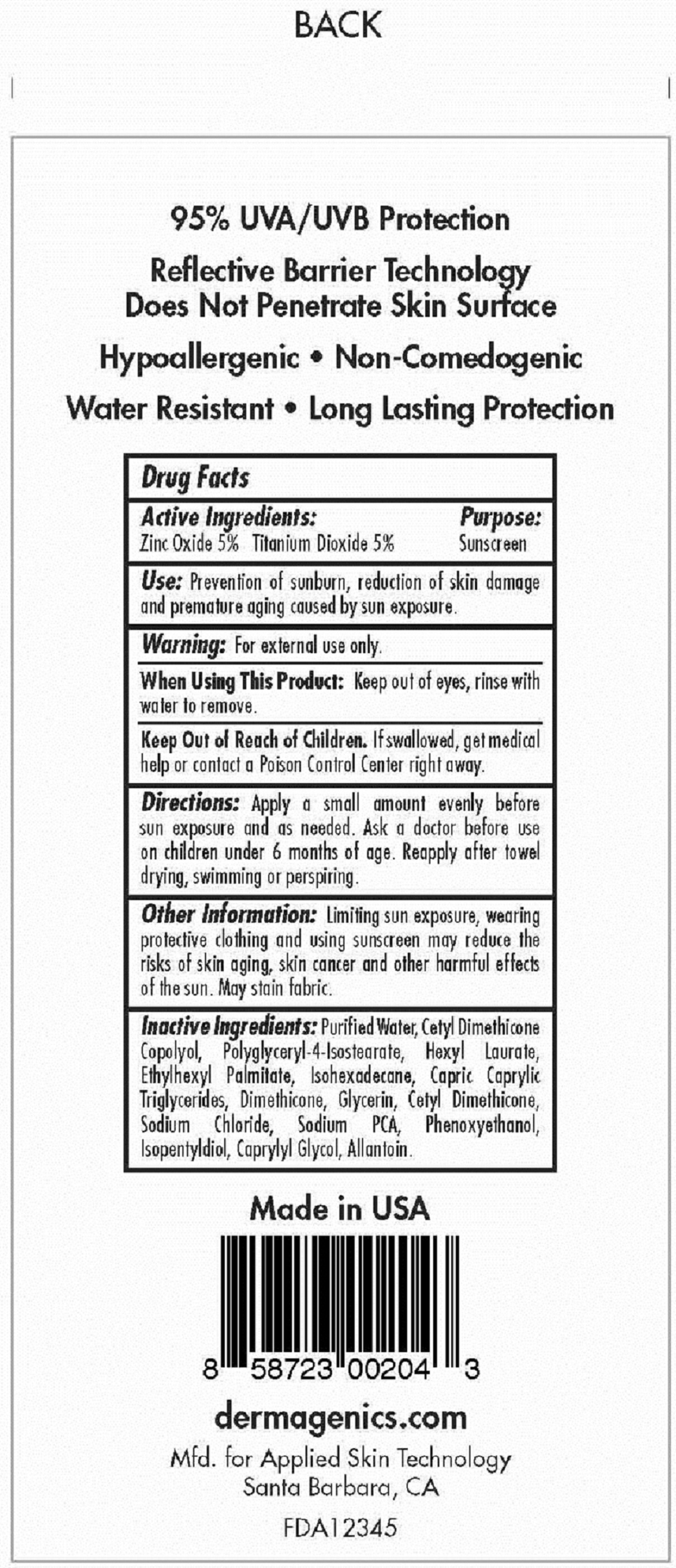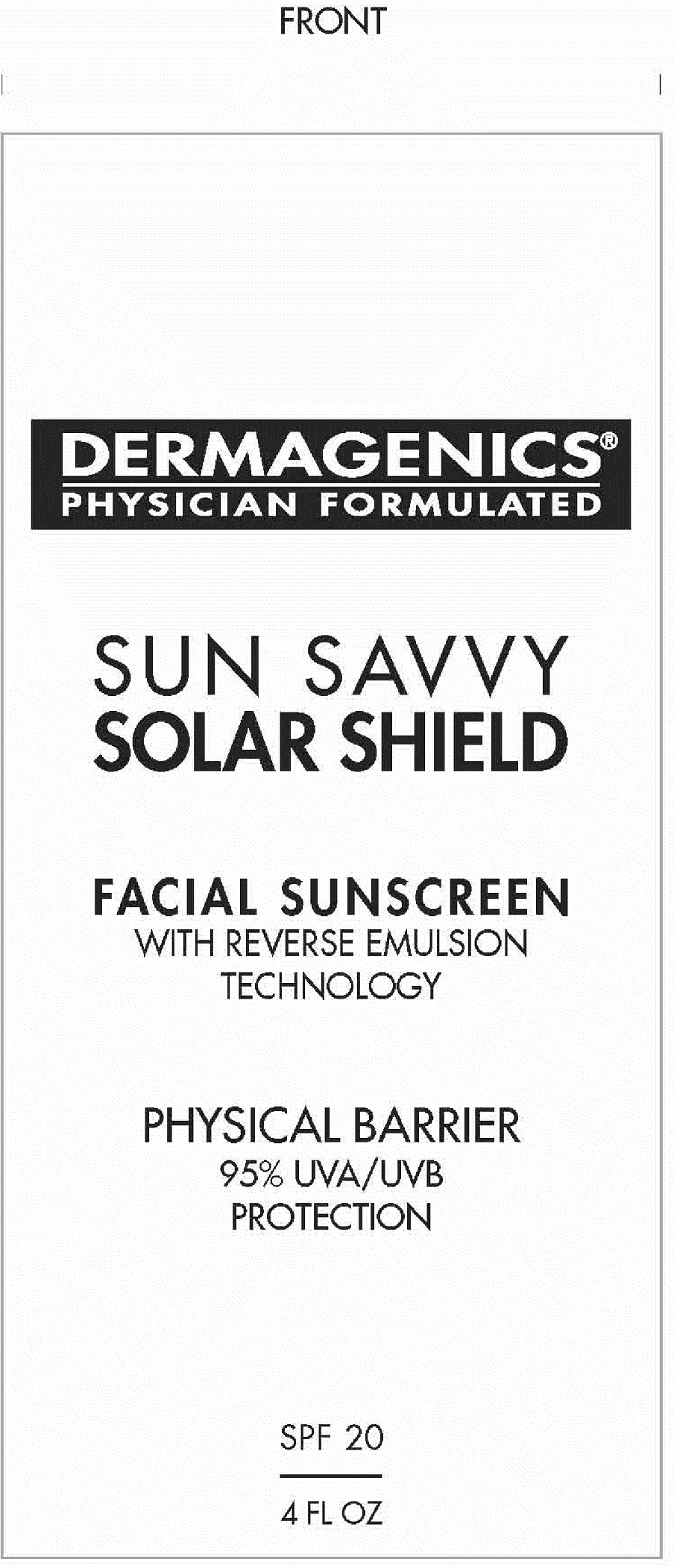 DRUG LABEL: SUN SAVVY SOLAR SHIELD
NDC: 55071-001 | Form: LOTION
Manufacturer: APPLIED SKIN TECHNOLOGY LLC
Category: otc | Type: HUMAN OTC DRUG LABEL
Date: 20111006

ACTIVE INGREDIENTS: ZINC OXIDE 5 g/100 mL; TITANIUM DIOXIDE 5 g/100 mL
INACTIVE INGREDIENTS: WATER; DIMETHICONE; POLYGLYCERYL-4 ISOSTEARATE; HEXYL LAURATE; ETHYLHEXYL PALMITATE; ISOHEXADECANE; MEDIUM-CHAIN TRIGLYCERIDES; GLYCERIN; SODIUM CHLORIDE; SODIUM PYRROLIDONE CARBOXYLATE; PHENOXYETHANOL; ISOPENTYLDIOL; CAPRYLYL GLYCOL; ALLANTOIN

SUN SAVVY SOLAR SHIELD SPF 20

ACTIVE INGREDIENTS:
ZINC OXIDE 5% TITANIUM DIOXIDE 5%

PURPOSE:
SUNSCREEN

INDICATIONS AND USAGE

USES: PREVENTION OF SUNBURN, REDUCTION OF SKIN DAMAGE AND PREMATURE AGING CAUSED BY SUN EXPOSURE.

WARNINGS

WARNING: FOR EXTERNAL USE ONLY.

WHEN USING THIS PRODUCT: KEEP OUT OF EYES, RINSE WITH WATER TO REMOVE.

KEEP OUT OF REACH OF CHILDREN. IF SWALLOWED GET MEDICAL HELP OR CONTACT A POISON CONTROL CENTER RIGHT AWAY.

DOSAGE AND ADMINISTRATION

DIRECTIONS: APPLY A SMALL AMOUNT EVENLY BEFORE SUN EXPOSURE AND AS NEEDED. ASK A DOCTOR BEFORE USE ON CHILDREN UNDER 6 MONTHS OF AGE. REAPPLY AFTER TOWEL DRYING, SWIMMING OR PERSPIRING.

OTHER INFORMATION: LIMITING SUN EXPOSURE, WEARING PROTECTIVE CLOTHING AND USING SUNSCREEN MAY REDUCE THE RISKS OF SKIN AGING, SKIN CANCER AND OTHER HARMFUL AFFECTS OF THE SUN. MAY STAIN FABRIC.

INACTIVE INGREDIENT

INACTIVE INGREDIENTS: PURIFIED WATER, CETYL DIMETHICONE COPOLYOL, POLYGLYCERYL-4 ISOSTEARATE, HEXYL LAURATE, ETHYLHEXYL PALMITATE, ISOHEXADECANE, CAPRIC CAPRYLIC TRIGLYCERIDES, DIMETHICONE, CETYL DIMETHICONE, SODIUM CHLORIDE, SODIUM PCA, PHENOXYETHANOL, ISOPENTYLDIOL, CAPRYLYL GLYCOL, ALLANTOIN.

PACKAGE LABEL

DERMAGENICS
PHYSICIAN FORMULATED
SUN SAVVY
SOLAR SHIELD
FACIAL SUNSCREEN
WITH REVERSE EMULSION
TECHNOLOGY
PHYSICAL BARRIER
95% UVA/UVB
PROTECTION
SPF 20
4 FL OZ